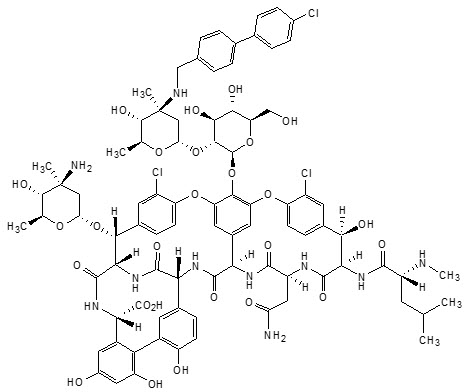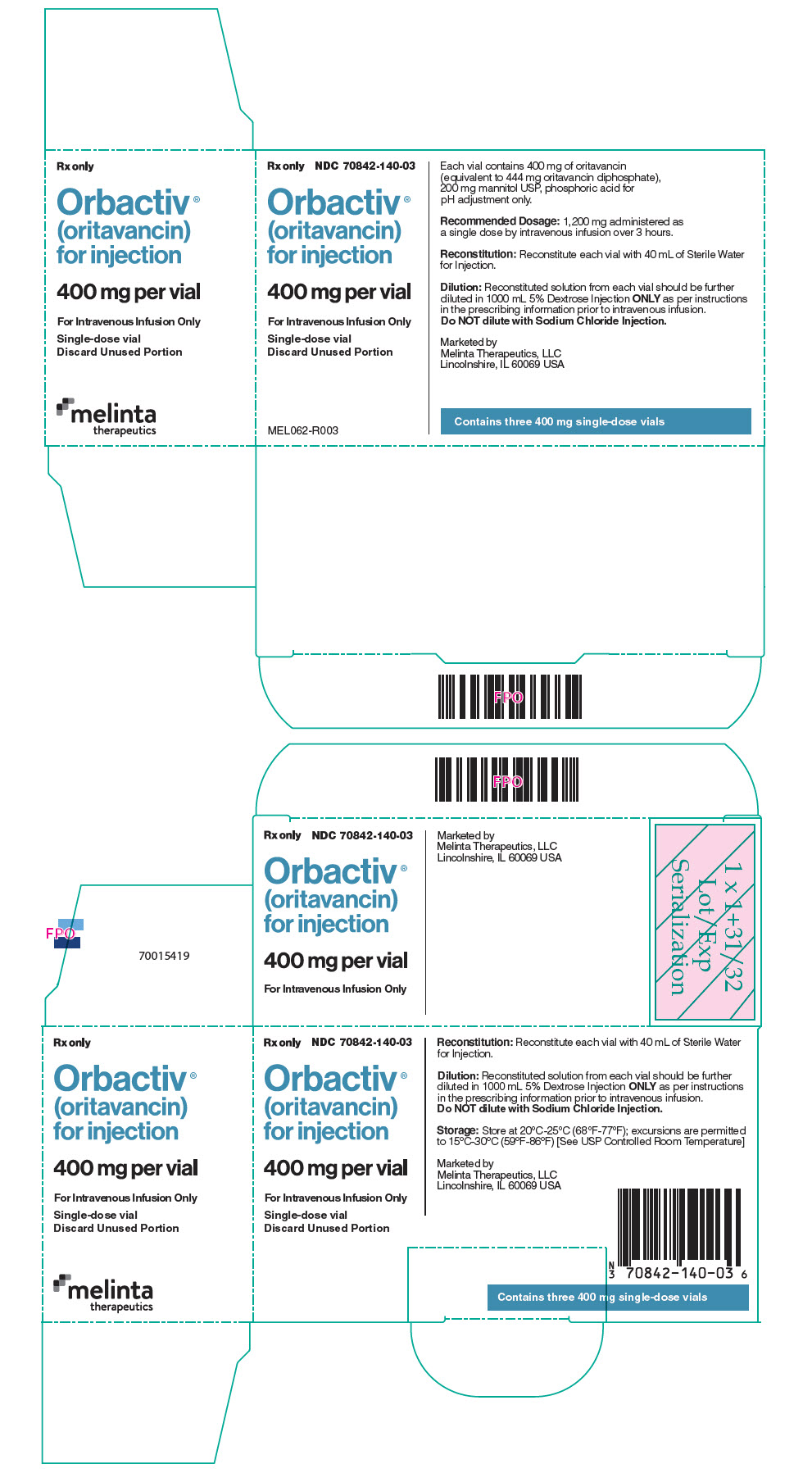 DRUG LABEL: Orbactiv
NDC: 70842-140 | Form: INJECTION, POWDER, LYOPHILIZED, FOR SOLUTION
Manufacturer: Melinta Therapeutics, LLC
Category: prescription | Type: HUMAN PRESCRIPTION DRUG LABEL
Date: 20250717

ACTIVE INGREDIENTS: ORITAVANCIN 400 mg/1 1
INACTIVE INGREDIENTS: MANNITOL; PHOSPHORIC ACID

HIGHLIGHTS OF PRESCRIBING INFORMATION

These highlights do not include all the information needed to use ORBACTIV safely and effectively. See full prescribing information for ORBACTIV.
ORBACTIV® (oritavancin) for injection, for intravenous use
Initial U.S. Approval: 2014

1 INDICATIONS AND USAGE

ORBACTIV is a lipoglycopeptide antibacterial drug indicated for the treatment of adult patients with acute bacterial skin and skin structure infections caused or suspected to be caused by susceptible isolates of designated Gram-positive microorganisms. (1.1)

To reduce the development of drug-resistant bacteria and maintain the effectiveness of ORBACTIV and other antibacterial drugs, ORBACTIV should be used only to treat or prevent infections that are proven or strongly suspected to be caused by bacteria. (1.2)

2 DOSAGE AND ADMINISTRATION

- There are two oritavancin products (ORBACTIV and KIMYRSA™, another oritavancin product) that have differences in dose strength, duration of infusion and preparation instructions, including reconstitution and dilution instructions and compatible diluents (2.1, 2.2, 2.3, 2.4)
- Administer 1,200 mg of ORBACTIV as a single dose by intravenous infusion over 3 hours. (2.1, 5.3)
- Carefully follow the recommended dosage and dose preparation instructions for ORBACTIV in the full prescribing information. (2.1, 2.2, 2.3)

3 DOSAGE FORMS AND STRENGTHS

For injection: 400 mg of lyophilized powder in a single-dose vial for reconstitution. (3)

4 CONTRAINDICATIONS

- Use of intravenous unfractionated heparin sodium is contraindicated for 120 hours (5 days) after ORBACTIV administration. (4.1, 5.1)
- Known hypersensitivity to oritavancin products. (4.2, 5.2)

5 WARNINGS AND PRECAUTIONS

- Coagulation test interference: ORBACTIV has been shown to artificially prolong aPTT for up to 120 hours, and may prolong PT and INR for up to 12 hours and ACT for up to 24 hours. For patients who require aPTT monitoring within 120 hours of ORBACTIV dosing, consider a non-phospholipid dependent coagulation test such as a Factor Xa (chromogenic) assay or an alternative anticoagulant not requiring aPTT. (5.1, 7.2)
- Serious hypersensitivity reactions, including anaphylaxis, have been reported with the use of oritavancin products, including ORBACTIV. Discontinue infusion if signs of acute hypersensitivity occur. Carefully monitor patients with known hypersensitivity to glycopeptides. (5.2)
- Infusion Related Reactions: Administer ORBACTIV over 3 hours to minimize infusion. Infusion related reactions have been reported with the glycopeptide class of antimicrobial agents, including oritavancin products (e.g. ORBACTIV). Stopping or slowing the infusion may result in cessation of these reactions. (5.3)
- Clostridioides difficile-associated diarrhea: Evaluate patients if diarrhea occurs. (5.4)
- Concomitant warfarin use: ORBACTIV has been shown to artificially prolong PT/INR for up to 12 hours (5.1). Patients should be monitored for bleeding if concomitantly receiving ORBACTIV and warfarin. (5.5)
- Osteomyelitis: Institute appropriate alternate antibacterial therapy in patients with confirmed or suspected osteomyelitis. (5.6)

6 ADVERSE REACTIONS

The most common adverse reactions (≥3%) in patients treated with ORBACTIV were headache, nausea, vomiting, limb and subcutaneous abscesses, and diarrhea. (6.1)

To report SUSPECTED ADVERSE REACTIONS, contact Melinta Therapeutics at 1-844-633-6568 or FDA at 1-800-FDA-1088 or www.fda.gov/medwatch.

FULL PRESCRIBING INFORMATION

1 INDICATIONS AND USAGE

1.1 Acute Bacterial Skin and Skin Structure Infections

ORBACTIV® (oritavancin) is indicated for the treatment of adult patients with acute bacterial skin and skin structure infections (ABSSSI) caused by susceptible isolates of the following Gram-positive microorganisms:

Staphylococcus aureus (including methicillin-susceptible and methicillin-resistant isolates), Streptococcus pyogenes, Streptococcus agalactiae, Streptococcus dysgalactiae, Streptococcus anginosus group (includes S. anginosus, S. intermedius, and S. constellatus), and Enterococcus faecalis (vancomycin-susceptible isolates only).

1.2 Usage

To reduce the development of drug-resistant bacteria and maintain the effectiveness of ORBACTIV and other antibacterial drugs, ORBACTIV should be used only to treat or prevent infections that are proven or strongly suspected to be caused by susceptible bacteria. When culture and susceptibility information are available, they should be considered in selecting or modifying antibacterial therapy. In the absence of such data, local epidemiology and susceptibility patterns may contribute to the empiric selection of therapy.

2 DOSAGE AND ADMINISTRATION

2.1 Dosage and Administration Overview

There are two oritavancin products (ORBACTIV and KIMYRSA™, another oritavancin product) that:

- Are supplied in different dose strengths of oritavancin [see Dosage Forms and Strengths (3)].
- Have different recommended durations of infusion [see Dosage and Administration (2.2)].
- Have different preparation instructions, including differences in reconstitution, dilution, and compatible diluents [see Dosage and Administration (2.3, 2.4)].

Carefully follow the recommended dosage and dose preparation instructions for ORBACTIV in this prescribing information (PI) [see Dosage and Administration (2.1, 2.2, 2.3, 2.4)]. Refer to the KIMYRSA prescribing information for relevant information of the other oritavancin product.

2.2 Recommended Dosage

The recommended dosage of ORBACTIV is 1,200 mg administered as a single dose by intravenous infusion over 3 hours in patients 18 years and older [see Warnings and Precautions (5.3)].

2.3 Preparation of ORBACTIV for Intravenous Infusion

There are two oritavancin products (ORBACTIV and KIMYRSA, another oritavancin product) that have differences in dose strengths, duration of infusion, reconstitution and dilution instructions, and compatible diluents. Carefully follow the reconstitution, and dilution instructions with the appropriate compatible diluent for ORBACTIV specified in this prescribing information. Refer to the KIMYRSA prescribing information for relevant information of the other oritavancin product.

ORBACTIV is intended for intravenous infusion, only after reconstitution and dilution.

Three ORBACTIV 400 mg vials need to be reconstituted and diluted to prepare a single 1,200 mg intravenous dose.

Reconstitution: Aseptic technique should be used to reconstitute three ORBACTIV 400 mg vials.

- Add 40 mL of sterile water for injection (WFI) to reconstitute each vial to provide a 10 mg/mL solution per vial.
- For each vial, gently swirl the contents to avoid foaming and ensure that all ORBACTIV powder is completely dissolved to form a reconstituted solution.
- Parenteral drug products should be inspected visually for particulate matter and discoloration prior to administration, whenever solution and container permit. Each reconstituted vial should appear to be a clear, colorless to pale yellow solution, free of visible particles.

Dilution: Use ONLY 5% dextrose injection (D5W) for dilution to prepare the final intravenous solution for infusion. Do NOT use Sodium Chloride Injection for dilution as it is incompatible with ORBACTIV and may cause precipitation of the drug. Since no preservative or bacteriostatic agent is present in ORBACTIV, aseptic technique must be used in preparing the final intravenous solution as follows:

- Withdraw and discard 120 mL from a 1000 mL intravenous bag of D5W.
- Withdraw 40 mL from each of the three reconstituted vials of ORBACTIV and add to D5W intravenous bag to bring the bag volume to 1000 mL. This yields a concentration of 1.2 mg/mL.

Discard any unused portion of the reconstituted solution remaining in each vial.

Storage and Use of Intravenous Solution: Diluted intravenous solution in an infusion bag should be used within 6 hours when stored at room temperature, or used within 12 hours when refrigerated at 2 to 8°C (36 to 46°F). The combined storage time (reconstituted solution in the vial and diluted solution in the bag) and 3 hour infusion time should not exceed 6 hours at room temperature or 12 hours if refrigerated.

2.4 Compatibility

ORBACTIV solution for administration by 3-hour infusion is ONLY compatible with:

- 5% dextrose injection (D5W)

2.5 Incompatibilities

ORBACTIV is administered intravenously. ORBACTIV should only be diluted in D5W. Do NOT use sodium chloride injection for dilution as it is incompatible with ORBACTIV and may cause precipitation of the drug. Therefore other intravenous substances, additives or other medications mixed in sodium chloride injection should not be added to ORBACTIV single-dose vials or infused simultaneously through the same IV line or through a common intravenous port.

In addition, drugs formulated at a basic or neutral pH may be incompatible with ORBACTIV. ORBACTIV should not be administered simultaneously with commonly used intravenous drugs through a common intravenous port. If the same intravenous line is used for sequential infusion of additional medications, the line should be flushed before and after infusion of ORBACTIV with D5W.

3 DOSAGE FORMS AND STRENGTHS

ORBACTIV is supplied as sterile, white to off-white lyophilized powder containing 400 mg of oritavancin (as oritavancin diphosphate) in a single-dose clear glass vial, which must be reconstituted and further diluted prior to intravenous administration.

4 CONTRAINDICATIONS

4.1 Intravenous Unfractionated Heparin Sodium

Use of intravenous unfractionated heparin sodium is contraindicated for 120 hours (5 days) after ORBACTIV administration because the activated partial thromboplastin time (aPTT) test results may remain falsely elevated for up to 120 hours (5 days) after ORBACTIV administration [see Warnings and Precautions (5.1) and Drug Interactions (7.2)].

4.2 Hypersensitivity

ORBACTIV is contraindicated in patients with known hypersensitivity to oritavancin products.

5 WARNINGS AND PRECAUTIONS

5.1 Coagulation Test Interference

ORBACTIV has been shown to artificially prolong aPTT for up to 120 hours, PT and INR for up to 12 hours, and activated clotting time (ACT) for up to 24 hours following administration of a single 1,200 mg dose by binding to and preventing action of the phospholipid reagents commonly used in laboratory coagulation tests. ORBACTIV has also been shown to elevate D-dimer concentrations up to 72 hours after ORBACTIV administration.

For patients who require aPTT monitoring within 120 hours of ORBACTIV dosing, a non-phospholipid dependent coagulation test such as a Factor Xa (chromogenic) assay or an alternative anticoagulant not requiring aPTT monitoring may be considered [see Contraindications (4.1) and Drug Interactions (7.2)].

ORBACTIV has no effect on the coagulation system in vivo.

5.2 Hypersensitivity

Serious hypersensitivity reactions, including anaphylaxis, have been reported with the use of oritavancin products, including ORBACTIV. If an acute hypersensitivity reaction occurs during ORBACTIV infusion, discontinue ORBACTIV immediately and institute appropriate supportive care. Before using ORBACTIV, inquire carefully about previous hypersensitivity reactions to glycopeptides. Due to the possibility of cross-sensitivity, carefully monitor for signs of hypersensitivity during ORBACTIV infusion in patients with a history of glycopeptide allergy. In the Phase 3 ABSSSI clinical trials, the median onset of hypersensitivity reactions in ORBACTIV-treated patients was 1.2 days and the median duration of these reactions was 2.4 days [see Adverse Reactions (6.1)].

5.3 Infusion Related Reactions

ORBACTIV is administered as a single dose by intravenous infusion, using a total infusion time of 3 hours to minimize the risk of infusion-related reactions. Infusion related reactions have been reported with the glycopeptide class of antimicrobial agents, including oritavancin products (e.g. ORBACTIV), including flushing of the upper body, urticaria, pruritus and/or rash [see Adverse Reactions (6.1)]. Infusion reactions characterized by chest pain, back pain, chills and tremor have been observed with the use of ORBACTIV, including after the administration of more than one dose of ORBACTIV during a single course of therapy.

Stopping or slowing the infusion may result in cessation of these reactions. The safety and effectiveness of more than one dose of ORBACTIV during a single course of therapy have not been established [see Dosage and Administration (2.2)].

5.4 Clostridioides difficile-associated Diarrhea

Clostridioides difficile-associated diarrhea (CDAD) has been reported for nearly all systemic antibacterial drugs, including ORBACTIV, and may range in severity from mild diarrhea to fatal colitis. Treatment with antibacterial agents alters the normal flora of the colon and may permit overgrowth of C. difficile.

C. difficile produces toxins A and B which contribute to the development of CDAD. Hypertoxin-producing strains of C. difficile cause increased morbidity and mortality, as these infections can be refractory to antibacterial therapy and may require colectomy. CDAD must be considered in all patients who present with diarrhea following antibacterial use. Careful medical history is necessary because CDAD has been reported to occur more than 2 months after the administration of antibacterial agents.

If CDAD is suspected or confirmed, antibacterial use not directed against C. difficile may need to be discontinued. Appropriate fluid and electrolyte management, protein supplementation, antibacterial treatment of C. difficile, and surgical evaluation should be instituted as clinically indicated.

5.5 Potential Risk of Bleeding with Concomitant Use of Warfarin

ORBACTIV has been shown to artificially prolong prothrombin time (PT) and international normalized ratio (INR) for up to 12 hours, making the monitoring of the anticoagulation effect of warfarin unreliable up to 12 hours after an ORBACTIV dose [see Warnings and Precautions (5.1)].

Patients should be monitored for bleeding if concomitantly receiving ORBACTIV and warfarin [see Drug Interactions (7.1)].

5.6 Osteomyelitis

In Phase 3 ABSSSI clinical trials, more cases of osteomyelitis were reported in the ORBACTIV treated arm than in the vancomycin-treated arm. Monitor patients for signs and symptoms of osteomyelitis. If osteomyelitis is suspected or diagnosed, institute appropriate alternate antibacterial therapy [see Adverse Reactions (6.1)].

5.7 Development of Drug Resistant Bacteria

Prescribing ORBACTIV in the absence of a proven or strongly suspected bacterial infection or a prophylactic indication is unlikely to provide benefit to the patient and increases the risk of the development of drug-resistant bacteria [see Patient Counseling Information (17)].

6 ADVERSE REACTIONS

The following adverse reactions are also discussed in the Warnings and Precautions section of labeling:

Hypersensitivity Reactions [see Warnings and Precautions (5.2)]

Infusion Related Reactions [see Warnings and Precautions (5.3)]

Clostridioides difficile-associated Diarrhea [see Warnings and Precautions (5.4)]

Osteomyelitis [see Warnings and Precautions (5.6)]

6.1 Clinical Trials Experience

Because clinical trials are conducted under widely varying conditions, adverse reaction rates observed in the clinical trials of ORBACTIV cannot be directly compared to rates in the clinical trials of another drug and may not reflect the rates observed in practice.

ORBACTIV has been evaluated in two, double-blind, controlled ABSSSI clinical trials, which included 976 adult patients treated with a single 1,200 mg intravenous dose of ORBACTIV and 983 patients treated with intravenous vancomycin for 7 to 10 days. The median age of patients treated with ORBACTIV was 45.6 years, ranging between 18 and 89 years of age with 8.8% ≥65 years of age. Patients treated with ORBACTIV were predominantly male (65.4%), 64.4% were Caucasian, 5.8% were African American, and 28.1% were Asian. Safety was evaluated for up to 60 days after dosing.

In the pooled ABSSSI clinical trials, serious adverse reactions were reported in 57/976 (5.8%) patients treated with ORBACTIV and 58/983 (5.9%) treated with vancomycin. The most commonly reported serious adverse reaction was cellulitis in both treatment groups: 11/976 (1.1%) in ORBACTIV and 12/983 (1.2%) in the vancomycin arms, respectively.

The most commonly reported adverse reactions (≥3%) in patients receiving a single 1,200 mg dose of ORBACTIV in the pooled ABSSSI clinical trials were: headache, nausea, vomiting, limb and subcutaneous abscesses, and diarrhea.

In the pooled ABSSSI clinical trials, ORBACTIV was discontinued due to adverse reactions in 36/976 (3.7%) of patients; the most common reported reactions leading to discontinuation were cellulitis (4/976, 0.4%) and osteomyelitis (3/976, 0.3%).

Table 1 provides selected adverse reactions occurring in ≥1.5% of patients receiving ORBACTIV in the pooled ABSSSI clinical trials. There were 540 (55.3%) patients in the ORBACTIV arm and 559 (56.9%) patients in the vancomycin arm, who reported ≥1 adverse reaction.

Table 1: Incidence of Selected Adverse Reactions Occurring in ≥1.5% of Patients Receiving ORBACTIV in the Pooled ABSSSI Clinical Trials
Adverse Reactions | ORBACTIV N=976 (%) | Vancomycin N=983 (%)
Gastrointestinal disorders
Diarrhea | 36 (3.7) | 32 (3.4)
Nausea | 97 (9.9) | 103 (10.5)
Vomiting | 45 (4.6) | 46 (4.7)
Nervous system disorders
Dizziness | 26 (2.7) | 26 (2.6)
Headache | 69 (7.1) | 66 (6.7)
General disorders and administration
Infusion site phlebitis | 24 (2.5) | 15 (1.5)
Infusion site reaction | 19 (1.9) | 34 (3.5)
Infections and infestations
Abscess (limb and subcutaneous) | 37 (3.8) | 23 (2.3)
Investigations
Alanine aminotransferase increased | 27 (2.8) | 15 (1.5)
Aspartate aminotransferase increased | 18 (1.8) | 15 (1.5)
Cardiac disorders
Tachycardia | 24 (2.5) | 11 (1.1)

The following selected adverse reactions were reported in ORBACTIV-treated patients at a rate of less than 1.5%:

Blood and lymphatic system disorders: anemia, eosinophilia

General disorders and administration site conditions: infusion site erythema, extravasation, induration, pruritus, rash, edema peripheral

Immune system disorders: hypersensitivity

Infections and infestations: osteomyelitis

Investigations: total bilirubin increased, hyperuricemia

Metabolism and nutrition disorders: hypoglycemia

Musculoskeletal and connective tissue disorders: tenosynovitis, myalgia

Respiratory, thoracic and mediastinal disorders: bronchospasm, wheezing

Skin and subcutaneous tissue disorders: urticaria, angioedema, erythema multiforme, pruritus, leucocytoclastic vasculitis, rash

6.2 Immunogenicity

There is potential for immunogenicity following administration of oritavancin products, including ORBACTIV. The detection of antibody formation is highly dependent on the sensitivity and specificity of the assay. Because several factors in an assay may influence the observed incidence of antibody positivity, comparison of the incidence of antibodies to oritavancin in the studies described below with the incidence of antibodies in other studies or to other products may be misleading.

Positive indirect and direct antiglobulin tests (IAT/DAT) were noted with the administration of ORBACTIV and KIMYRSA (hereinafter referred to as another oritavancin product) in studies with healthy subjects and patients with ABSSSI. In a randomized, open-label, multi-center ABSSSI study, positive antiglobulin tests were reported in 9.6% (5/52) of subjects who received ORBACTIV and 2% (1/50) of subjects who received another oritavancin product. Oritavancin-dependent RBC antibodies were detected when tested in the presence of drug for three subjects in the ORBACTIV group.

In a multiple dose study with ORBACTIV in healthy volunteers, 90% (9/10) of subjects had a positive IAT 14 days after the second infusion.

In a healthy volunteer study, 66% (22/32) of subjects receiving another oritavancin product had a positive IAT 15 days after receiving dosing and one subject had a positive DAT at 8 days after dosing.

There were no reports of hemolysis in subjects who had positive IAT/DAT. If hemolytic anemia develops following treatment with ORBACTIV provide appropriate care. Positive IAT may interfere with cross-matching before blood transfusion [see Drug Interactions (7.2)].

7 DRUG INTERACTIONS

7.1 Effect of ORBACTIV on CYP Substrates

A screening drug-drug interaction study indicated that ORBACTIV is a nonspecific, weak inhibitor (CYP2C9 and CYP2C19) or inducer (CYP3A4 and CYP2D6) of several CYP isoforms [see Clinical Pharmacology (12.3)]. A drug-drug interaction study that assessed the interaction potential of a single 1,200 mg dose of ORBACTIV on the pharmacokinetics of S-warfarin (CYP2C9 probe substrate) showed no effect of ORBACTIV on S-warfarin Cmax or AUC.

Avoid administering ORBACTIV concomitantly with drugs that are predominantly metabolized by one of the affected CYP450 enzymes, as co-administration may increase or decrease concentrations of those drugs. Patients should be closely monitored for signs of toxicity or lack of efficacy if they have been given ORBACTIV while on a potentially affected compound (e.g. patients should be monitored for bleeding if concomitantly receiving ORBACTIV and warfarin).

7.2 Drug-Laboratory Test Interactions

Prolongation of Certain Laboratory Coagulation Tests

ORBACTIV may artificially prolong certain laboratory coagulation tests (see Table 2) by binding to and preventing the action of the phospholipid reagents which activate coagulation in commonly used laboratory coagulation tests [see Contraindications (4.1) and Warnings and Precautions (5.1, 5.5)]. For patients who require monitoring of anticoagulation effect within the indicated time after ORBACTIV dosing, a non-phospholipid dependent coagulation test such as a Factor Xa (chromogenic) assay or an alternative anticoagulant not requiring aPTT monitoring may be considered.

ORBACTIV does not interfere with coagulation in vivo. In addition, ORBACTIV does not affect tests that are used for diagnosis of Heparin Induced Thrombocytopenia (HIT).

Table 2: Coagulation Tests Affected and Unaffected by ORBACTIV
Elevated by ORBACTIV | Unaffected by ORBACTIV
Prothrombin time (PT) up to 12 hours | Chromogenic Factor Xa Assay
International normalized ratio (INR) up to 12 hours | Thrombin Time (TT)
Activated partial thromboplastin time (aPTT) up to 120 hours
Activated clotting time (ACT) up to 24 hours
Silica clot time (SCT) up to 18 hours
Dilute Russell's viper venom time (DRVVT) up to 72 hours
D-dimer up to 72 hours

Positive Indirect and Direct Antiglobulin Tests (IAT/DAT)

Positive IAT/DAT were noted with administration of oritavancin products, including ORBACTIV, in studies with healthy volunteers and patients with ABSSSI. Positive IAT may interfere with cross-matching before blood transfusion [see Adverse Reactions (6.2)].

8 USE IN SPECIFIC POPULATIONS

8.1 Pregnancy

Risk Summary

There are no available data on ORBACTIV use in pregnant women to evaluate for a drug- associated risk of major birth defects, miscarriage or adverse maternal or fetal outcomes. In animal reproduction studies, no effects on embryo-fetal development or survival were observed in pregnant rats or rabbits treated at the highest doses throughout organogenesis with intravenous oritavancin, at doses equivalent to 25% of the single clinical dose of 1,200 mg (see Data).

The estimated background risk of major birth defects and miscarriage for the indicated population is unknown. All pregnancies have a background risk of birth defect, loss, or other adverse outcomes. In the U.S. general population, the estimated background risk of major birth defects and miscarriage in clinically recognized pregnancies is 2% to 4% and 15% to 20%, respectively.

Data

Animal Data

Reproduction studies performed in rats and rabbits have revealed no evidence of harm to the fetus due to oritavancin at the highest doses administered throughout organogenesis, 30 mg/kg/day (gestation days 6-17) and 15 mg/kg/day (gestation days 7-19), respectively. Those doses would be equivalent to a human dose of 300 mg, or 25% of the single clinical dose of 1,200 mg. Higher doses were not evaluated in nonclinical developmental and reproductive toxicology studies.

8.2 Lactation

Risk Summary

There are no data on the presence of oritavancin in human milk, the effects on the breastfed- child, or the effects on milk production. ORBACTIV is present in the breast milk of rats (see Data). When a drug is present in animal milk, it is likely that the drug will be present in human milk.

The developmental and health benefits of breastfeeding should be considered along with the mother's clinical need for ORBACTIV and any potential adverse effects on the breast-fed child from ORBACTIV or from the underlying maternal condition.

Data

Following a single intravenous infusion in lactating rats, radio-labeled [^14C]-oritavancin was excreted in milk and absorbed by nursing pups.

8.4 Pediatric Use

Safety and effectiveness of ORBACTIV in pediatric patients (younger than 18 years of age) have not been established.

8.5 Geriatric Use

The pooled Phase 3 ABSSSI clinical trials of ORBACTIV did not include sufficient numbers of subjects aged 65 and older to determine whether they respond differently from younger subjects. Other reported clinical experience has not identified differences in responses between the elderly and younger patients, but greater sensitivity of some older individuals cannot be ruled out.

8.6 Renal Impairment

No dosage adjustment of ORBACTIV is needed in patients with mild or moderate renal impairment [see Clinical Pharmacology (12.3)]. The pharmacokinetics of ORBACTIV in severe renal impairment have not been evaluated. ORBACTIV is not removed from blood by hemodialysis.

8.7 Hepatic Impairment

No dosage adjustment of ORBACTIV is needed in patients with mild or moderate hepatic impairment. The pharmacokinetics of ORBACTIV in patients with severe hepatic insufficiency has not been studied [see Dosage and Administration (2.2), Clinical Pharmacology (12.3)].

10 OVERDOSAGE

In the ORBACTIV clinical program there was no incidence of accidental overdose of ORBACTIV.

Based on an in vitro hemodialysis study, ORBACTIV is unlikely to be removed from blood by hemodialysis. In the event of overdose, supportive measures should be taken.

11 DESCRIPTION

ORBACTIV (oritavancin) for injection contains oritavancin diphosphate, a semisynthetic lipoglycopeptide antibacterial drug for intravenous infusion.

The chemical name for oritavancin is [4"R]-22-O-(3-amino-2,3,6-trideoxy-3-C-methyl-α-L-arabino-hexopyranosyl)-N3''-[(4'-chloro[1,1'-biphenyl]-4-yl)methyl] vancomycin phosphate [1:2] [salt]. The empirical formula of oritavancin diphosphate is C86H97N10O26Cl3∙2H3PO4 and the molecular weight is 1989.09. The chemical structure is represented below:

∙2H3PO4

ORBACTIV for injection is supplied as a sterile white to off-white lyophilized powder in a single-dose clear glass vial that contains 400 mg of oritavancin (equivalent to 444 mg oritavancin diphosphate) and the following inactive ingredients: mannitol (200 mg) and phosphoric acid (to adjust pH 3.1 to 4.3).

Each vial is reconstituted with sterile water for injection and further diluted with 5% dextrose injection (D5W) for intravenous infusion. Both the reconstituted solution and the diluted solution for infusion should be a clear, colorless to pale yellow solution, free of visible particles [see Dosage and Administration (2.3)].

12 CLINICAL PHARMACOLOGY

12.1 Mechanism of Action

Oritavancin is an antibacterial drug [see Microbiology (12.4)].

12.2 Pharmacodynamics

The antimicrobial activity of oritavancin appears to correlate with the ratio of area under the concentration-time curve to minimal inhibitory concentration (AUC/MIC) based on animal models of infection.

Exposure-response analyses from both preclinical and clinical studies support the treatment of clinically relevant Gram-positive microorganisms (e.g. S. aureus and S. pyogenes) causative of ABSSSI with a single 1,200 mg dose of ORBACTIV.

Cardiac Electrophysiology

In a thorough QTc study of 135 healthy subjects at a dose 1.3 times the 1,200 mg recommended dose, ORBACTIV did not prolong the QTc interval to any clinically relevant extent.

12.3 Pharmacokinetics

The population PK analysis was derived using data from the two Phase 3 ABSSSI clinical trials in 297 patients. The mean (±SD) pharmacokinetic parameters of oritavancin in patients following a single 1,200 mg dose are presented in Table 3.

Table 3: Mean (±SD) PK parameters for patients receiving a single ORBACTIV 1,200 mg dose for ABSSSI (n=297)
Parameter | Mean (±SD)
Cmax (µg/mL) | 138 (±31.7)
AUC0-24 (µg∙h/mL) | 1110 (±378)
AUC0-∞ (µg∙h/mL) | 2800 (±801)
Cmax, Maximum plasma concentration; AUC0-24, Area under the plasma concentration-time curve from time zero to 24 hours, AUC0-∞, Area under the plasma concentration time curve from time zero to infinity; SD, Standard Deviation.

Oritavancin exhibits linear pharmacokinetics at a dose up to 1,200 mg. The mean, population-predicted oritavancin concentration-time profile displays a multi-exponential decline with a long terminal plasma half-life.

Distribution

Oritavancin is approximately 85% bound to human plasma proteins.

Based on population PK analysis, the population mean total volume of distribution is estimated to be approximately 87.6 L, indicating oritavancin is extensively distributed into the tissues.

Exposures of oritavancin in skin blister fluid were approximately 20% of those in plasma (AUC0-24) after single 800 mg dose in healthy subjects.

Metabolism/Excretion

Non-clinical studies including in vitro human liver microsome studies indicated that oritavancin is not metabolized. No mass balance study has been conducted in humans. In humans, oritavancin is slowly excreted unchanged in feces and urine with less than 1% and 5% of the dose recovered in feces and urine, respectively, after 2 weeks of collection.

Oritavancin has a terminal half-life of approximately 245 hours and a clearance of 0.445 L/h based on population pharmacokinetic analyses.

Specific Populations

No dosage adjustments of ORBACTIV are required for patients with mild to moderate renal or mild to moderate hepatic impairment or other subpopulations including age, gender, race and weight.

Renal Impairment

The pharmacokinetics of oritavancin were examined in the Phase 3 ABSSSI trials in patients with normal renal function, CrCL ≥80 mL/min (n=238), mild renal impairment, CrCL 50-79 mL/min (n=48), and moderate renal impairment, CrCL 30-49 mL/min (n=11). Population pharmacokinetic analysis indicated that mild to moderate renal impairment had no clinically relevant effect on the exposure of oritavancin. No dedicated studies in dialysis patients have been conducted.

Dosage adjustment of ORBACTIV is not needed in patients with mild or moderate renal impairment. The pharmacokinetics of oritavancin in patients with severe renal impairment have not been evaluated.

Hepatic Impairment

The pharmacokinetics of oritavancin were evaluated in study of subjects with moderate hepatic impairment (Child-Pugh Class B) (n=20) and compared with healthy subjects (n=20) matched for gender, age and weight. There were no relevant changes in pharmacokinetics of oritavancin in subjects with moderate hepatic impairment.

Dosage adjustment of ORBACTIV is not needed in patients with mild or moderate hepatic impairment. The pharmacokinetics of oritavancin in patients with severe hepatic insufficiency has not been studied.

Age, Gender, Weight and Race

Population pharmacokinetic analysis from the Phase 3 ABSSSI trials in patients indicated that gender, age, weight or race had no clinically relevant effect on the exposure of ORBACTIV. No dosage adjustment of ORBACTIV is warranted in these subpopulations.

Drug Interactions

In vitro studies with human liver microsomes showed that oritavancin inhibited the activities of cytochrome P450 (CYP) enzymes 1A2, 2B6, 2D6, 2C9, 2C19, and 3A4. The observed inhibition of multiple CYP isoforms by oritavancin in vitro is likely to be reversible and noncompetitive. In vitro studies indicate that oritavancin is neither a substrate nor an inhibitor of the efflux transporter P-glycoprotein (P-gp).

Drugs that Inhibit or Induce CYP450 Enzymes

A screening drug-drug interaction study was conducted in healthy volunteers (n=16) evaluating the concomitant administration of a single 1,200 mg dose of ORBACTIV with probe substrates for several CYP450 enzymes. The results showed that ORBACTIV is a weak inducer of CYP3A4 (a decrease of 18% in the mean AUC of midazolam) and CYP2D6 (decrease of 31% in the ratio of dextromethorphan to dextrorphan concentrations in the urine after administration of dextromethorphan). ORBACTIV was also a weak inhibitor of CYP2C19 (increase of 15% in the ratio of omeprazole to 5-OH-omeprazole concentrations in the plasma after administration of omeprazole) and also showed to be a weak inhibitor of CYP2C9 (with an increase of 31% in the mean AUC of warfarin) [see Warnings and Precautions (5.5), and Drug Interactions (7.1)].

In the screening drug-drug interaction study, co-administration of ORBACTIV resulted in an increase of 18% in the ratio of 1-methylxanthine + 1 methylurate + 5-acetylamino-6-formylamino-3-methyluracil (1X + 1U + AFMU) to 1,7-dimethylurate (17U) concentrations in the urine after administration of caffeine (CYP1A2 probe substrate), and an increase of 16% in the ratio of AFMU to (1X +1U) concentrations in the urine after administration of caffeine (N-Acetyltransferase- 2 probe substrate). Co-administration of ORBACTIV did not change the mean systemic exposure of caffeine metabolite (Xanthine oxidase probe substrate).

A study to assess the drug-drug interaction potential of a single 1,200 mg dose of ORBACTIV on the pharmacokinetics of S-warfarin following a single dose was conducted in 36 healthy subjects. S-warfarin pharmacokinetics were evaluated following a single dose of warfarin 25 mg given alone, or administered at the start, 24, or 72 hours after a single 1,200 mg ORBACTIV dose. The results showed no effect of ORBACTIV on S-warfarin Cmax or AUC.

12.4 Microbiology

ORBACTIV is a semi-synthetic, lipoglycopeptide antibacterial drug. ORBACTIV exerts a concentration-dependent bactericidal activity in vitro against S. aureus, S. pyogenes, and E. faecalis.

Mechanism of Action

Oritavancin has three mechanisms of action: (i) inhibition of the transglycosylation (polymerization) step of cell wall biosynthesis by binding to the stem peptide of peptidoglycan precursors; (ii) inhibition of the transpeptidation (crosslinking) step of cell wall biosynthesis by binding to the peptide bridging segments of the cell wall; and (iii) disruption of bacterial membrane integrity, leading to depolarization, permeabilization, and cell death. These multiple mechanisms contribute to the concentration-dependent bactericidal activity of oritavancin.

Resistance

In serial passage studies, resistance to oritavancin was observed in isolates of S. aureus and E. faecalis. Resistance to oritavancin was not observed in clinical studies.

Interaction with Other Antimicrobial Agents

In in vitro studies, oritavancin exhibits synergistic bactericidal activity in combination with gentamicin, moxifloxacin or rifampicin against isolates of methicillin-susceptible S. aureus (MSSA), with gentamicin or linezolid against isolates of heterogeneous vancomycin-intermediate S. aureus (hVISA), VISA, and vancomycin-resistant S. aureus (VRSA), and with rifampin against isolates of VRSA. In vitro studies demonstrated no antagonism between oritavancin and gentamicin, moxifloxacin, linezolid or rifampin.

Antibacterial Activity

Oritavancin has been shown to be active against most isolates of the following microorganisms, both in vitro and in clinical infections [see Indications and Usage (1.1)].

Gram-positive Bacteria

Staphylococcus aureus (including methicillin-resistant isolates)

Streptococcus agalactiae

Streptococcus anginosus group (includes S. anginosus, S. intermedius, and S. constellatus)

Streptococcus dysgalactiae

Streptococcus pyogenes

Enterococcus faecalis (vancomycin-susceptible isolates only)

The following in vitro data are available, but their clinical significance is unknown. At least 90 percent of the following bacteria exhibit an in vitro minimum inhibitory concentration (MIC) less than or equal to the susceptible breakpoint for oritavancin against isolates of a similar organism group. However, the efficacy of oritavancin in treating clinical infections due to these bacteria has not been established in adequate and well-controlled clinical trials.

Gram-positive Bacteria

Enterococcus faecium (vancomycin-susceptible isolates only)

Susceptibility Testing Methods

For specific information regarding susceptibility test interpretive criteria and associated test methods and quality control standards recognized by FDA for this drug, please see: https://www.fda.gov/STIC.

13 NONCLINICAL TOXICOLOGY

13.1 Carcinogenesis, Mutagenesis, Impairment of Fertility

Long term studies in animals have not been conducted to determine the carcinogenic potential of oritavancin.

No mutagenic or clastogenic potential of oritavancin was found in a battery of tests, including an Ames assay, in vitro chromosome aberration assay in Chinese hamster ovary cells, in vitro forward mutation assay in mouse lymphoma cells and an in vivo mouse micronucleus assay.

Oritavancin did not affect the fertility or reproductive performance of male rats (exposed to daily doses up to 30 mg/kg for at least 4 weeks) and female rats (exposed to daily doses up to 30 mg/kg for at least 2 weeks prior to mating). Those daily doses would be equivalent to a human dose of 300 mg, or 25% of clinical dose. Higher doses were not evaluated in nonclinical fertility studies.

14 CLINICAL STUDIES

14.1 Acute Bacterial Skin and Skin Structure Infections (ABSSSI)

A total of 1987 adults with clinically documented ABSSSI suspected or proven to be due to Gram-positive pathogens were randomized into two identically designed, randomized, double-blind, multi-center, multinational, non-inferiority trials (Trial 1 and Trial 2) comparing a single 1,200 mg intravenous dose of ORBACTIV to intravenous vancomycin (1 g or 15 mg/kg every 12 hours) for 7 to 10 days. The primary analysis population (modified intent to treat, mITT) included all randomized patients who received any study drug. Patients could receive concomitant aztreonam or metronidazole for suspected Gram-negative and anaerobic infection, respectively. Patient demographic and baseline characteristics were balanced between treatment groups. Approximately 64% of patients were Caucasian and 65% were males. The mean age was 45 years and the mean body mass index was 27 kg/m^2. Across both trials, approximately 60% of patients were enrolled from the United States and 27% of patients from Asia. A history of diabetes was present in 14% of patients. The types of ABSSSI across both trials included cellulitis/erysipelas (40%), wound infection (29%), and major cutaneous abscesses (31%). Median infection area at baseline across both trials was 266.6 cm^2. The primary endpoint in both trials was early clinical response (responder), defined as cessation of spread or reduction in size of baseline lesion, absence of fever, and no rescue antibacterial drug at 48 to 72 hours after initiation of therapy.

Table 4 provides the efficacy results for the primary endpoint in Trial 1 and Trial 2 in the primary analysis population.

Table 4: Clinical Response Rates in ABSSSI Trials using Responders [Cessation of spread or reduction in size of baseline lesion, absence of fever (<37.7°C) and no rescue antibacterial drug at 48 to 72 hours.] , [Patients who died at 48 to 72 hours, after initiation of therapy or who had increase in lesion size at 48 to 72 hours, after initiation of therapy or who used non-study antibacterial therapy during first 72 hours or who had an additional, unplanned, surgical procedure or who had missing measurements during the first 72 hours from initiation of study drug were classified as non-responders.] at 48-72 Hours after Initiation of Therapy
 | ORBACTIV n /N (%) | Vancomycin n /N (%) | Difference (95% CI) [95% CI based on the Normal approximation to Binomial distribution.]
Trial 1 | 391/475 (82.3) | 378/479 (78.9) | 3.4 (-1.6, 8.4)
Trial 2 | 403/503 (80.1) | 416/502 (82.9) | -2.7 (-7.5, 2.0)

A key secondary endpoint in these two ABSSSI trials evaluated the percentage of patients achieving a 20% or greater reduction in lesion area from baseline at 48-72 hours after initiation of therapy. Table 5 summarizes the findings for this endpoint in the two ABSSSI trials.

Table 5: Clinical Response Rates [Patients who died at 48 to 72 hours, after initiation of therapy or who had increase in lesion size at 48 to 72 hours, after initiation of therapy or who used non-study antibacterial therapy during first 72 hours or who had an additional, unplanned, surgical procedure or who had missing measurements during the first 72 hours from initiation of study drug were classified as non-responders.] in ABSSSI Trials using Reduction in Lesion Area of 20% or Greater at 48-72 Hours after Initiation of Therapy
 | ORBACTIV n /N (%) | Vancomycin n /N (%) | Difference (95% CI) [95% CI based on the Normal approximation to Binomial distribution.]
Trial 1 | 413/475 (86.9) | 397/479 (82.9) | 4.1 (-0.5, 8.6)
Trial 2 | 432/503 (85.9) | 428/502 (85.3) | 0.6 (-3.7, 5.0)

Another secondary efficacy endpoint in the two trials was investigator-assessed clinical success at post therapy evaluation at Day 14 to 24 (7 to 14 days from end of blinded therapy). A patient was categorized as a clinical success if the patient experienced a complete or nearly complete resolution of baseline signs and symptoms related to primary ABSSSI site (erythema, induration/edema, purulent drainage, fluctuance, pain, tenderness, local increase in heat/warmth) such that no further treatment with antibacterial drugs was needed.

Table 6 summarizes the findings for this endpoint in the mITT and clinically evaluable population in these two ABSSSI trials. Note that there are insufficient historical data to establish the magnitude of drug effect for antibacterial drugs compared with placebo at the post therapy visits. Therefore, comparisons of ORBACTIV to vancomycin based on clinical success rates at these visits cannot be utilized to establish non-inferiority conclusions.

Table 6: Clinical Success Rates [Clinical success was defined if the patient experienced a complete or nearly complete resolution of baseline signs and symptoms as described above.] in ABSSSI Trials at the Follow-Up Visit (7-14 days after end of therapy)
 | ORBACTIV n /N (%) | Vancomycin n /N (%) | Difference (95% CI) [95% CI based on the Normal approximation to Binomial distribution.]
Trial 1
mITT [mITT population consisted of all randomized patients who received study drug; CE population consisted of all mITT patients who did not have violations of inclusion and exclusion criteria, completed treatment and had investigator assessment at the Follow-Up Visit.] | 378/475 (79.6) | 383/479 (80.0) | -0.4 (-5.5, 4.7)
CE | 362/394 (91.9) | 370/397 (93.2) | -1.3 (-5.0,2.3)
Trial 2
mITT | 416/503 (82.7) | 404/502 (80.5) | 2.2 (-2.6, 7.0)
CE | 398/427 (93.2) | 387/408 (94.9) | -1.6 (-4.9,1.6)

Outcomes by Baseline Pathogen: Table 7 shows outcomes in patients with an identified baseline pathogen in the microbiological Intent-to-Treat (microITT) population in a pooled analysis of Trial 1 and Trial 2. The outcomes shown in the table are clinical response rates at 48 to 72 hours and clinical success rates at follow-up study day 14 to 24.

Table 7: Outcomes by Baseline Pathogen (microITT)
 | At 48-72 hours |  |  |  | Study day 14 to 24
 | Early Clinical Responder [Early clinical response defined as a composite of the cessation of spread or reduction in size of baseline lesion, absence of fever and no rescue antibacterial drug at 48-72 hours.] |  | ≥ 20% reduction in lesion size [Patients achieving a 20% or greater reduction in lesion area from baseline at 48-72 hours after initiation of therapy.] |  | Clinical Success [Clinical success was defined if the patient experienced a complete or nearly complete resolution of baseline signs and symptoms as described above.]
Pathogen [Baseline bacteremia in the oritavancin arm with relevant microorganisms causing ABSSSI included four subjects with MSSA and seven subjects with MRSA. Eight of these eleven subjects were responders at 48 to 72 hours after initiation of therapy.] | ORBACTIV n/N (%) | Vancomycin n/N (%) | ORBACTIV n/N (%) | Vancomycin n/N (%) | ORBACTIV n/N (%) | Vancomycin n/N (%)
Staphylococcus aureus | 388/472 (82.2) | 395/473 (83.5) | 421/472 (89.2) | 407/473 (86.0) | 390/472 (82.6) | 398/473 (84.1)
Methicillin-susceptible | 222/268 (82.8) | 233/272 (85.7) | 231/268 (86.2) | 232/272 (85.3) | 220/268 (82.1) | 229/272 (84.2)
Methicillin-resistant | 166/204 (81.4) | 162/201 (80.6) | 190/204 (93.1) | 175/201 (87.1) | 170/204 (83.3) | 169/201 (84.1)
Streptococcus pyogenes | 21/31 (67.7) | 23/32 (71.9) | 24/31 (77.4) | 24/32 (75.0) | 25/31 (80.6) | 23/32 (71.9)
Streptococcus agalactiae | 7/8 (87.5) | 12/12 (100.0) | 8/8 (100.0) | 12/12 (100.0) | 7/8 (87.5) | 11/12 (91.7)
Streptococcus dysgalactiae | 7/9 (77.8) | 6/6 (100.0) | 6/9 (66.7) | 5/6 (83.3) | 7/9 (77.8) | 3/6 (50.0)
Streptococcus anginosus group | 28/33 (84.8) | 40/45 (88.9) | 29/33 (87.9) | 42/45 (93.3) | 25/33 (75.8) | 38/45 (84.4)
Enterococcus faecalis | 11/13 (84.6) | 10/12 (83.3) | 10/13 (76.9) | 8/12 (66.7) | 8/13 (61.5) | 9/12 (75.0)

16 HOW SUPPLIED/STORAGE AND HANDLING

16.1 How Supplied/Storage

ORBACTIV is supplied as a sterile white to off-white lyophilized powder in single-dose clear glass vials containing 400 mg of oritavancin (NDC 70842-140-01), packaged in a carton of 3 vials (NDC 70842-140-03).

ORBACTIV vials should be stored at 20°C to 25°C (68°F to 77°F); excursions permitted to 15°C to 30°C (59°F to 86°F) [see USP, Controlled Room Temperature (CRT)].

17 PATIENT COUNSELING INFORMATION

Allergic Reactions

Patients should be advised that allergic reactions, including serious allergic reactions, could occur and that serious reactions require immediate treatment. They should inform their healthcare provider about any previous hypersensitivity reactions to oritavancin products, other glycopeptides (vancomycin, telavancin, or dalbavancin) or other allergens.

Diarrhea

Patients should be advised that diarrhea is a common problem caused by antibacterial drugs including ORBACTIV, which usually resolves when the drug is discontinued. Sometimes, frequent watery or bloody diarrhea may occur and may be a sign of a more serious intestinal infection. If severe watery or bloody diarrhea develops, patients should contact their healthcare provider.

Development of Antibacterial Resistance

Patients should be counseled that antibacterial drugs including ORBACTIV should only be used to treat bacterial infections. They do not treat viral infections (e.g., the common cold). When ORBACTIV is prescribed to treat a bacterial infection, patients should be told that although it is common to feel better early in the course of therapy, the medication should be taken exactly as directed. Skipping doses or not completing the full course of therapy may (1) decrease the effectiveness of the immediate treatment and (2) increase the likelihood that bacteria will develop resistance and will not be treatable by ORBACTIV or other antibacterial drugs in the future.

Marketed By:
Melinta Therapeutics, LLC
Parsippany, NJ 07054 USA

©2025 Melinta Therapeutics, LLC. All rights reserved.

MEL060-R006

PRINCIPAL DISPLAY PANEL - 400 mg Vial Carton

Rx only
NDC 70842-140-03

Orbactiv®
(oritavancin)
for injection

400 mg per vial

For Intravenous Infusion Only

Single-dose vial
Discard Unused Portion

MEL062-R003

Each vial contains 400 mg of oritavancin
(equivalent to 444 mg oritavancin diphosphate),
200 mg mannitol USP, phosphoric acid for
pH adjustment only.

Recommended Dosage: 1,200 mg administered as
a single dose by intravenous infusion over 3 hours.

Reconstitution: Reconstitute each vial with 40 mL of Sterile Water
for Injection.

Dilution: Reconstituted solution from each vial should be further
diluted in 1000 mL 5% Dextrose Injection ONLY as per instructions
in the prescribing information prior to intravenous infusion.
Do NOT dilute with Sodium Chloride Injection.

Marketed by
Melinta Therapeutics, LLC
Lincolnshire, IL 60069 USA

Contains three 400 mg single-dose vials